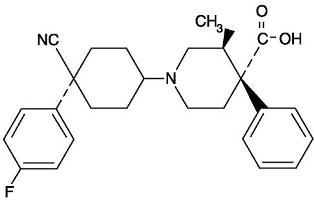 DRUG LABEL: Unknown
Manufacturer: Novartis Ophthalmics
Category: prescription | Type: HUMAN PRESCRIPTION DRUG LABELING
Date: 20060112

Livostin®

LIVOSTIN®

0.05% (levocabastine hydrochloride ophthalmic suspension)

DESCRIPTION

LIVOSTIN™ 0.05% (levocabastine hydrochloride ophthalmic suspension) is a selective histamine H1-receptor antagonist for topical ophthalmic use. Each mL contains 0.54 mg levocabastine hydrochloride equivalent to 0.5 mg levocabastine; 0.15 mg benzalkonium chloride; propylene glycol; polysorbate 80; dibasic sodium phosphate, anhydrous; monobasic sodium phosphate, monohydrate; disodium edetate; hydroxypropyl methylcellulose; and purified water. It has a pH of 6.0 to 8.0.

The chemical name for levocabastine hydrochloride is (–)-trans-1-[cis-4-Cyano-4- (p-fluorophenyl)cyclohexyl]-3-methyl-4-phenylisonipecotic acid monohydrochloride, and is represented by the following chemical structure:

● HCl

CLINICAL PHARMACOLOGY

Levocabastine is a potent, selective histamine H1-antagonist.

Antigen challenge studies performed two and four hours after initial drug instillation indicated activity was maintained for at least two hours.

In an environmental study, LIVOSTIN™ 0.05% (levocabastine hydrochloride ophthalmic suspension) instilled four times daily was shown to be significantly more effective than its vehicle in reducing ocular itching associated with seasonal allergic conjunctivitis.

After instillation in the eye, levocabastine is systemically absorbed. However, the amount of systemically absorbed levocabastine after therapeutic ocular doses is low (mean plasma concentrations in the range of 1-2 ng/mL).

INDICATIONS AND USAGE

LIVOSTIN™ 0.05% (levocabastine hydrochloride ophthalmic suspension) is indicated for the temporary relief of the signs and symptoms of seasonal allergic conjunctivitis.

CONTRAINDICATIONS

This product is contraindicated in persons with known or suspected hypersensitivity to any of its components. It should not be used while soft contact lenses are being worn.

WARNING

For topical use only. Not for injection.

PRECAUTIONS

Information for Patients

SHAKE WELL BEFORE USING. To prevent contaminating the dropper tip and suspension, care should be taken not to touch the eyelids or surrounding areas with the dropper tip of the bottle. Keep bottle tightly closed when not in use. Do not use if the suspension has discolored. Store at controlled room temperature. Protect from freezing.

Carcinogenesis, Mutagenesis, Impairment of Fertility

Levocabastine was not carcinogenic in male or female rats or in male mice when administered in the diet for up to 24 months. In female mice, levocabastine doses of 5,000 and 21,500 times the maximum recommended ocular human use level resulted in an increased incidence of pituitary gland adenoma and mammary gland adenocarcinoma possibly produced by increased prolactin levels. The clinical relevance of this finding is unknown with regard to the interspecies differences in prolactin physiology and the very low plasma concentrations of levocabastine following ocular administration.

Mutagenic potential was not demonstrated for levocabastine when tested in Ames’ Salmonella reversion test or in Escherichia coli, Drosophila melanogaster, a mouse Dominant Lethal Assay or in rat Micronucleus test.

In reproduction studies in rats, levocabastine showed no effects on fertility at oral doses of 20 mg/kg/day (8,300 times the maximum recommended human ocular dose).

PREGNANCY

Teratogenic Effects

Pregnancy Category C.

Levocabastine has been shown to be teratogenic (polydactyly) in rats when given in doses 16,500 times the maximum recommended human ocular dose. Teratogenicity (polydactyly, hydrocephaly, brachygnathia), embryotoxicity, and maternal toxicity were observed in rats at 66,000 times the maximum recommended ocular human dose. There are no adequate and well-controlled studies in pregnant women. Levocabastine should be used during pregnancy only if the potential benefit justifies the potential risk to the fetus.

Nursing Mothers

Based on determinations of levocabastine in breast milk after ophthalmic administration of the drug to one nursing woman, it was calculated that the daily dose of levocabastine in the infant was about 0.5 µg.

Pediatric Use

Safety and effectiveness in pediatric patients below the age of 12 have not been established.

ADVERSE REACTIONS

The most frequent adverse experiences reported with the use of LIVOSTIN™ 0.05% (levocabastine hydrochloride ophthalmic suspension) were mild, transient stinging and burning (29%) and headache (5%).

Other adverse experiences reported in approximately 1-3% of patients treated with LIVOSTIN™ were visual disturbances, dry mouth, fatigue, pharyngitis, eye pain/dryness, somnolence, red eyes, lacrimation/discharge, cough, nausea, rash/erythema, eyelid edema, and dyspnea.

DOSAGE AND ADMINISTRATION

SHAKE WELL BEFORE USING. The usual dose is one drop instilled in affected eyes four times per day.

HOW SUPPLIED

LIVOSTIN™ 0.05% (levocabastine hydrochloride ophthalmic suspension), 2.5 mL, 5 mL, and 10 mL is provided in white, polyethylene dropper tip squeeze bottles.

Keep tightly closed when not in use.

Do not use if the suspension has discolored.

Store at controlled room temperature 15°to 30°C (59° to 86°F).

Protect from freezing.

NDC 58768-610-10 (10.0 mL)

NDC 58768-610-05 (5.0 mL)

NDC 58768-610-99 (2.5 mL)

Rx Only

Levocabastine hydrochloride is an original product of Janssen Pharmaceutica Inc.

Mfd. by OMJ Pharmaceuticals, Inc.,

San Germán, P.R., 00683 for:

Novartis Ophthalmics, Duluth, GA 30097

5035-E